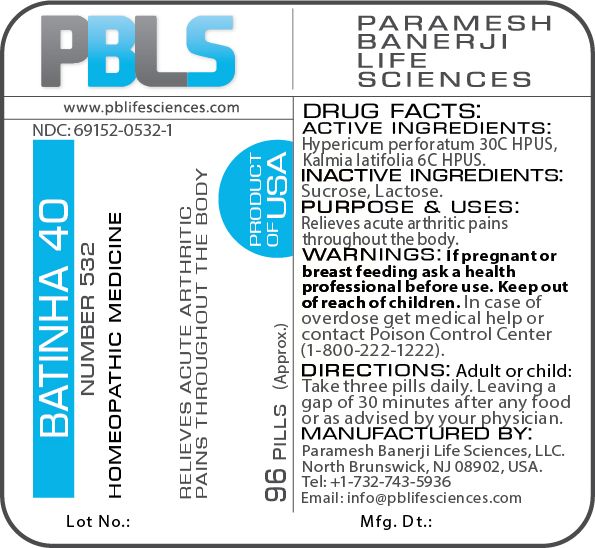 DRUG LABEL: Batinha 40 (Number 532)
NDC: 69152-0532 | Form: PELLET
Manufacturer: Paramesh Banerji Life Sciences LLC
Category: homeopathic | Type: HUMAN OTC DRUG LABEL
Date: 20180730

ACTIVE INGREDIENTS: HYPERICUM PERFORATUM 30 [hp_C]/1 1; KALMIA LATIFOLIA LEAF 6 [hp_C]/1 1
INACTIVE INGREDIENTS: SUCROSE; LACTOSE

DRUG FACTS: Active Ingredients

Hypericum perforatum 30C HPUS, Kalmia latifolia 6C HPUS

Inactive Ingredients

Sucrose, Lactose

Purpose

Relieves acute arthritic pains throughout the body

Uses

Relieves acute arthritic pains throughout the body

Warnings

If pregnant or breast feeding ask a health professional before use.

Keep out of reach of children. In case of overdose, get medical help or contact a Poison Control Center (1-800-222-1222) right away.

Direction

Adult or child: Take three pills daily. Leaving a gap of 30 minutes after any food or as advised by your physician.

Manufactured by

Paramesh Banerji Life Sciences, LLC.

North Brunswick, NJ 08902, USA.

Tel: +1-732-743-5936

Email: info@pblifesciences.com

Principal Display Panel

NDC: 69152-0532-1

Batinha 40

Number 532

Homeopathic Medicine

Relieves acute arthritic pains throughout the body

96 Pills (Approx.)

Product of USA